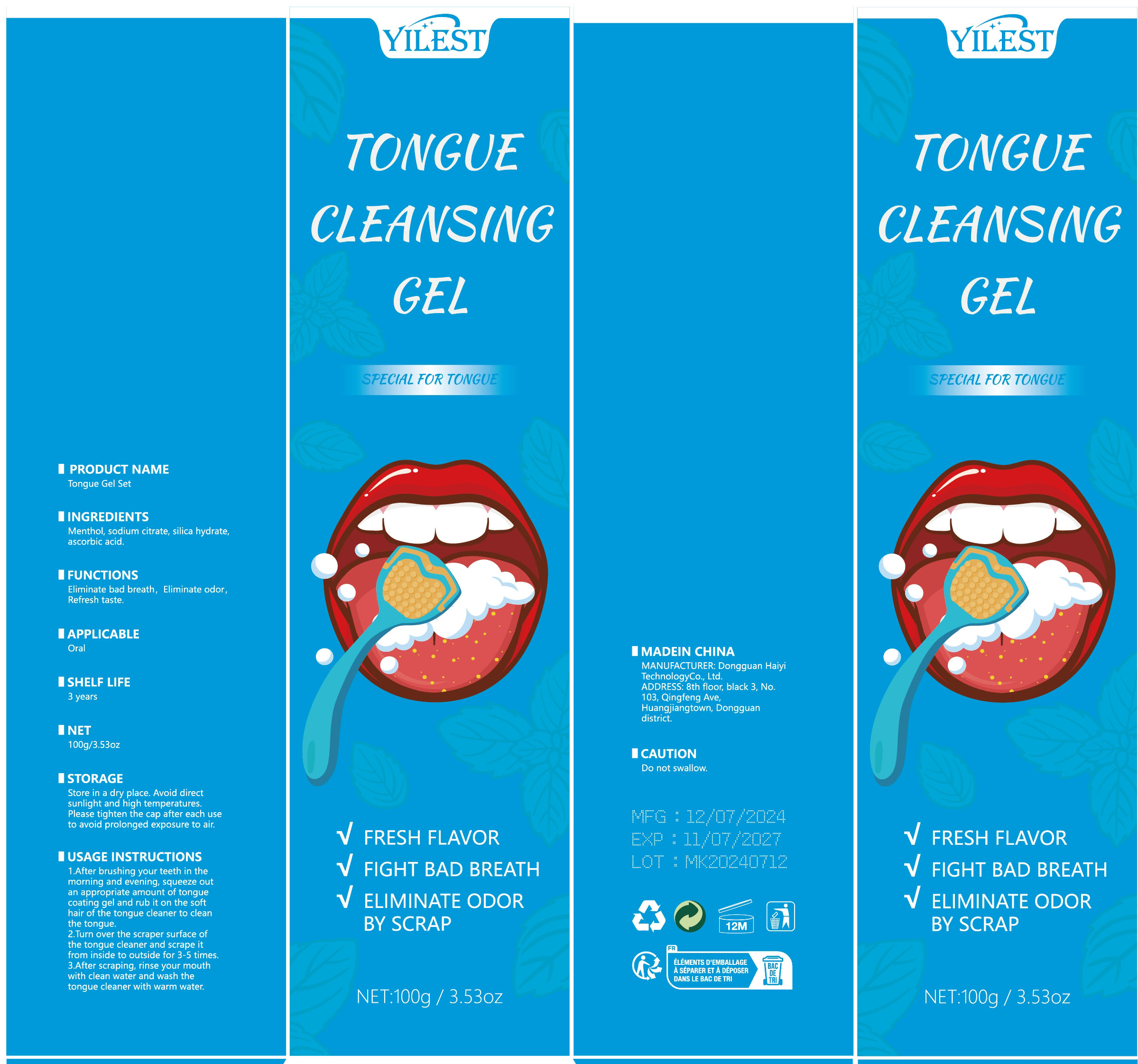 DRUG LABEL: Tongue Gel Set
NDC: 84732-091 | Form: PASTE
Manufacturer: Dongguan Haiyi Technology Co.,Ltd.
Category: otc | Type: HUMAN OTC DRUG LABEL
Date: 20241111

ACTIVE INGREDIENTS: SODIUM CITRATE 1 mg/100 g
INACTIVE INGREDIENTS: PRUNUS PERSICA (PEACH) FRUIT EXTRACT; ASCORBIC ACID; HYDRATED SILICA

Active ingredient

sodium citrate

Inactive ingredient

Prunus Persica (Peach) Fruit Extract,silica hydrate, ascorbicacid.

Purpose section

Eliminate bad breath, Eliminate odor,Refresh taste.

Warning

1).For external use only, avoid directcontact with eyes, lf you feel any
discomfort, stop using itand wash it with plenty of water. In severe cases,
pleaseseek medical attention in time.
2). Not allowed to be used ondamaged skin,

stop use

This product may cause allergic reactions in asmall number of people.
lf youexperience any discomfort,please stop using it immediately.

not use

Not suitable for use by children, pregnantor breast feeding people.

OUT OF CHILDREN

KEEP THE PRODUCT OUT OF REACH OF CHILDREN to

HOW TO USE

1.After brushing your teeth in themorning and evening, squeeze outan appropriate amount of tonguecoating gel and rub it on the softhair of the tongue cleaner to cleanthe tongue.

2.Turn over the scraper surface ofthe tongue cleaner and scrape itfrom inside to outside for 3-5 times.

3.After scraping, rinse your mouthwith clean water and wash thetongue cleaner with warm water.

Dosage

Once a day in the morning and evening